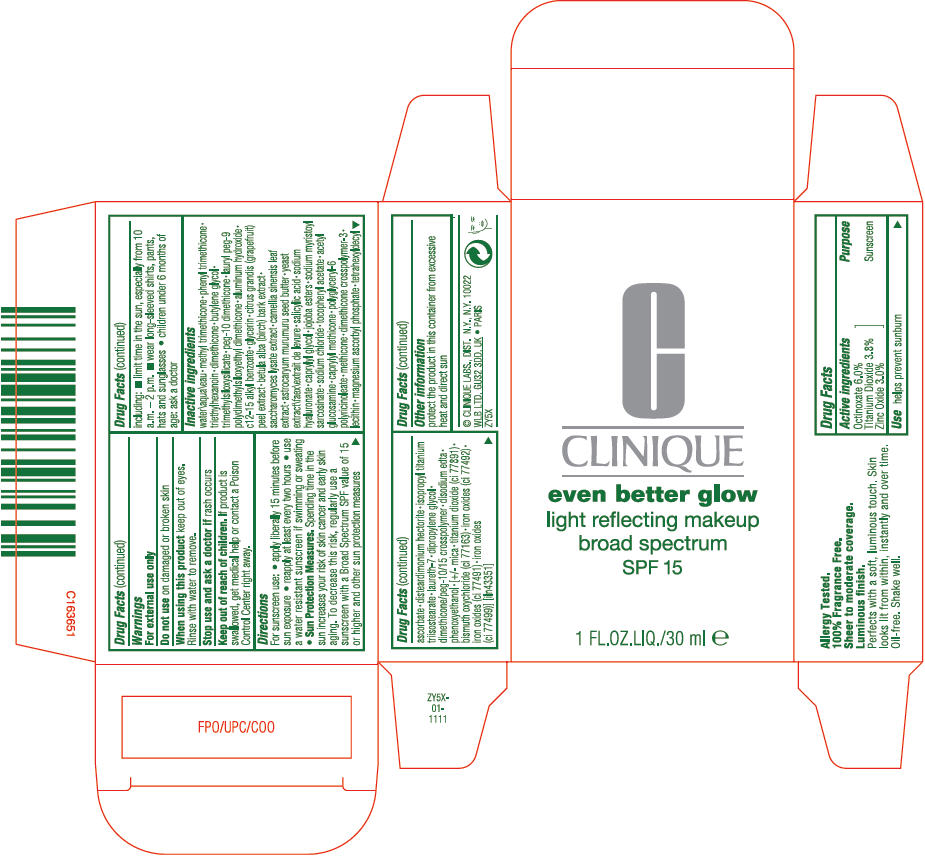 DRUG LABEL: EVEN BETTER GLOW LIGHT REFLECTING MAKEUP BROAD SPECTRUM SPF 15
NDC: 49527-056 | Form: LOTION
Manufacturer: CLINIQUE LABORATORIES LLC
Category: otc | Type: HUMAN OTC DRUG LABEL
Date: 20231005

ACTIVE INGREDIENTS: OCTINOXATE 60 mg/1 mL; TITANIUM DIOXIDE 38 mg/1 mL; ZINC OXIDE 30 mg/1 mL
INACTIVE INGREDIENTS: WATER; METHYL TRIMETHICONE; PHENYL TRIMETHICONE; TRIETHYLHEXANOIN; DIMETHICONE; BUTYLENE GLYCOL; PEG-10 DIMETHICONE (600 CST); LAURYL PEG-9 POLYDIMETHYLSILOXYETHYL DIMETHICONE; ALUMINUM HYDROXIDE; ALKYL (C12-15) BENZOATE; GLYCERIN; CITRUS MAXIMA FRUIT RIND; BETULA PUBESCENS BARK; SACCHAROMYCES LYSATE; GREEN TEA LEAF; ASTROCARYUM MURUMURU SEED BUTTER; YEAST, UNSPECIFIED; SALICYLIC ACID; HYALURONATE SODIUM; CAPRYLYL GLYCOL; SODIUM MYRISTOYL SARCOSINATE; SODIUM CHLORIDE; .ALPHA.-TOCOPHEROL ACETATE; N-ACETYLGLUCOSAMINE; CAPRYLYL TRISILOXANE; METHICONE (20 CST); MAGNESIUM ASCORBYL PHOSPHATE; TETRAHEXYLDECYL ASCORBATE; DISTEARDIMONIUM HECTORITE; ISOPROPYL TITANIUM TRIISOSTEARATE; LAURETH-7; DIPROPYLENE GLYCOL; EDETATE DISODIUM ANHYDROUS; PHENOXYETHANOL; MICA; BISMUTH OXYCHLORIDE; FERRIC OXIDE YELLOW; FERRIC OXIDE RED; FERROSOFERRIC OXIDE

EVEN BETTER GLOW LIGHT REFLECTING MAKEUP BROAD SPECTRUM SPF 15

Drug Facts

Active ingredients

Octinoxate 6.0%
Titanium Dioxide 3.8%
Zinc Oxide 3.0%

Purpose

Sunscreen

Use

helps prevent sunburn

Warnings

For external use only

Do not use on damaged or broken skin

When using this product keep out of eyes. Rinse with water to remove.

Stop use and ask a doctor if rash occurs

Keep out of reach of children. If product is swallowed, get medical help or contact a Poison Control Center right away.

Directions

For sunscreen use:

- apply liberally 15 minutes before sun exposure
- reapply at least every two hours
- use a water resistant sunscreen if swimming or sweating
- Sun Protection Measures. Spending time in the sun increases your risk of skin cancer and early skin aging. To decrease this risk, regularly use a sunscreen with a Broad Spectrum SPF value of 15 or higher and other sun protection measures including:
  - limit time in the sun, especially from 10 a.m. – 2 p.m.
  - wear long-sleeved shirts, pants, hats and sunglasses
- children under 6 months of age: ask a doctor

Inactive ingredients

water\aqua\eau • methyl trimethicone • phenyl trimethicone • triethylhexanoin • dimethicone • butylene glycol • trimethylsiloxysilicate • peg-10 dimethicone • lauryl peg-9 polydimethylsiloxyethyl dimethicone • aluminum hydroxide • c12-15 alkyl benzoate • glycerin • citrus grandis (grapefruit) peel extract • betula alba (birch) bark extract • saccharomyces lysate extract • camellia sinensis leaf extract • astrocaryum murumuru seed butter • yeast extract\faex\extrait de levure • salicylic acid • sodium hyaluronate • caprylyl glycol • jojoba esters • sodium myristoyl sarcosinate • sodium chloride • tocopheryl acetate • acetyl glucosamine • caprylyl methicone • polyglyceryl-6 polyricinoleate • methicone • dimethicone crosspolymer-3 • lecithin • magnesium ascorbyl phosphate • tetrahexyldecyl ascorbate • disteardimonium hectorite • isopropyl titanium triisostearate • laureth-7 • dipropylene glycol • dimethicone/peg-10/15 crosspolymer • disodium edta • phenoxyethanol • [+/- mica • titanium dioxide (ci 77891) • bismuth oxychloride (ci 77163) • iron oxides (ci 77492) • iron oxides (ci 77491) • iron oxides (ci 77499) [iln43351]

Other information

protect the product in this container from excessive heat and direct sun

PRINCIPAL DISPLAY PANEL - 30 ml Jar Carton

C

CLINIQUE

even better glow

light reflecting makeup
broad spectrum
SPF 15

1 FL.OZ.LIQ./30 ml e